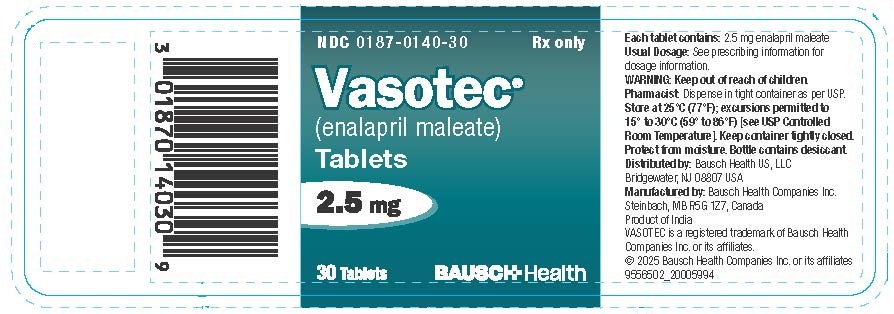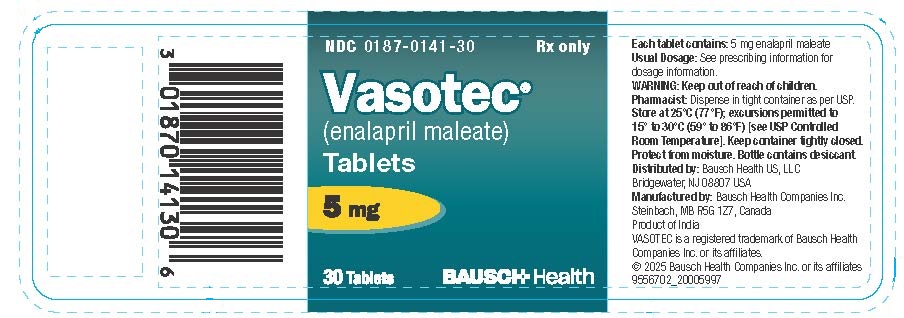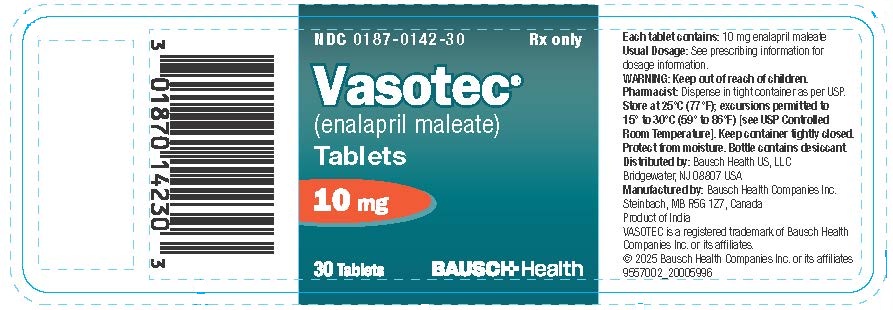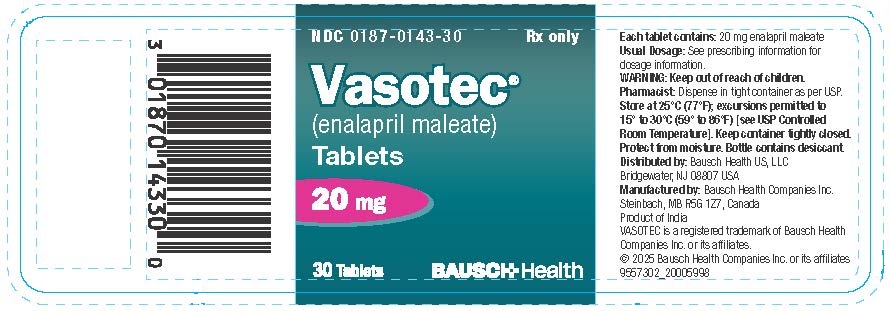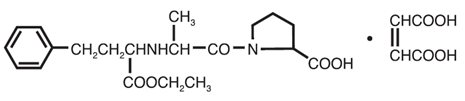 DRUG LABEL: Vasotec
NDC: 0187-0140 | Form: TABLET
Manufacturer: Bausch Health US LLC
Category: prescription | Type: HUMAN PRESCRIPTION DRUG LABEL
Date: 20260123

ACTIVE INGREDIENTS: Enalapril Maleate 2.5 mg/1 1
INACTIVE INGREDIENTS: LACTOSE, UNSPECIFIED FORM; magnesium stearate; sodium stearate; sodium bicarbonate; starch, corn

VASOTEC® (enalapril maleate) Tablets

WARNING: FETAL TOXICITY

See full prescribing information for complete boxed warning.

- When pregnancy is detected, discontinue VASOTEC® as soon as possible.
- Drugs that act directly on the renin-angiotensin system can cause injury and death to the developing fetus (see WARNINGS, Fetal Toxicity).

DESCRIPTION

VASOTEC® (enalapril maleate) is the maleate salt of enalapril, the ethyl ester of a long-acting angiotensin-converting enzyme inhibitor, enalaprilat. Enalapril maleate is chemically described as (S)-1-[N-[1-(ethoxycarbonyl)-3-phenylpropyl]-L-alanyl]-L-proline, (Z)-2-butenedioate salt (1:1). Its empirical formula is C20H28N2O5•C4H4O4, and its structural formula is:

Enalapril maleate is a white to off-white, crystalline powder with a molecular weight of 492.53. It is sparingly soluble in water, soluble in ethanol, and freely soluble in methanol.

Enalapril is a pro-drug; following oral administration, it is bioactivated by hydrolysis of the ethyl ester to enalaprilat, which is the active angiotensin-converting enzyme inhibitor.

Enalapril maleate is supplied as 2.5 mg, 5 mg, 10 mg, and 20 mg tablets for oral administration. In addition to the active ingredient enalapril maleate, each tablet contains the following inactive ingredients: lactose, magnesium stearate, sodium bicarbonate, and starch. The 10 mg and 20 mg tablets also contain iron oxides.

CLINICAL PHARMACOLOGY

Mechanism of Action

Enalapril, after hydrolysis to enalaprilat, inhibits angiotensin-converting enzyme (ACE) in human subjects and animals. ACE is a peptidyl dipeptidase that catalyzes the conversion of angiotensin I to the vasoconstrictor substance, angiotensin II. Angiotensin II also stimulates aldosterone secretion by the adrenal cortex. The beneficial effects of enalapril in hypertension and heart failure appear to result primarily from suppression of the renin-angiotensin-aldosterone system. Inhibition of ACE results in decreased plasma angiotensin II, which leads to decreased vasopressor activity and to decreased aldosterone secretion. Although the latter decrease is small, it results in small increases of serum potassium. In hypertensive patients treated with VASOTEC alone for up to 48 weeks, mean increases in serum potassium of approximately 0.2 mEq/L were observed. In patients treated with VASOTEC plus a thiazide diuretic, there was essentially no change in serum potassium (see PRECAUTIONS). Removal of angiotensin II negative feedback on renin secretion leads to increased plasma renin activity.

ACE is identical to kininase, an enzyme that degrades bradykinin. Whether increased levels of bradykinin, a potent vasodepressor peptide, play a role in the therapeutic effects of VASOTEC remains to be elucidated.

While the mechanism through which VASOTEC lowers blood pressure is believed to be primarily suppression of the renin-angiotensin-aldosterone system, VASOTEC is antihypertensive even in patients with low-renin hypertension. Although VASOTEC was antihypertensive in all races studied, black hypertensive patients (usually a low-renin hypertensive population) had a smaller average response to enalapril monotherapy than non-black patients.

Pharmacokinetics and Metabolism

Following oral administration of VASOTEC, peak serum concentrations of enalapril occur within about one hour. Based on urinary recovery, the extent of absorption of enalapril is approximately 60 percent. Enalapril absorption is not influenced by the presence of food in the gastrointestinal tract. Following absorption, enalapril is hydrolyzed to enalaprilat, which is a more potent angiotensin-converting enzyme inhibitor than enalapril; enalaprilat is poorly absorbed when administered orally. Peak serum concentrations of enalaprilat occur three to four hours after an oral dose of enalapril maleate. Excretion of VASOTEC is primarily renal. Approximately 94 percent of the dose is recovered in the urine and feces as enalaprilat or enalapril. The principal components in urine are enalaprilat, accounting for about 40 percent of the dose, and intact enalapril. There is no evidence of metabolites of enalapril, other than enalaprilat.

The serum concentration profile of enalaprilat exhibits a prolonged terminal phase, apparently representing a small fraction of the administered dose that has been bound to ACE. The amount bound does not increase with dose, indicating a saturable site of binding. The effective half-life for accumulation of enalaprilat following multiple doses of enalapril maleate is 11 hours. The disposition of enalapril and enalaprilat in patients with renal insufficiency is similar to that in patients with normal renal function until the glomerular filtration rate is 30 mL/min or less. With glomerular filtration rate ≤30 mL/min, peak and trough enalaprilat levels increase, time to peak concentration increases and time to steady state may be delayed. The effective half-life of enalaprilat following multiple doses of enalapril maleate is prolonged at this level of renal insufficiency (see DOSAGE AND ADMINISTRATION). Enalaprilat is dialyzable at the rate of 62 mL/min.

Studies in dogs indicate that enalapril crosses the blood-brain barrier poorly, if at all; enalaprilat does not enter the brain. Multiple doses of enalapril maleate in rats do not result in accumulation in any tissues. Milk of lactating rats contains radioactivity following administration of ^14C-enalapril maleate. Radioactivity was found to cross the placenta following administration of labeled drug to pregnant hamsters.

Pharmacodynamics and Clinical Effects

Hypertension

Administration of VASOTEC to patients with hypertension of severity ranging from mild to severe results in a reduction of both supine and standing blood pressure usually with no orthostatic component. Symptomatic postural hypotension is therefore infrequent, although it might be anticipated in volume-depleted patients (see WARNINGS, Hypotension).

In most patients studied, after oral administration of a single dose of enalapril, onset of antihypertensive activity was seen at one hour with peak reduction of blood pressure achieved by four to six hours.

At recommended doses, antihypertensive effects have been maintained for at least 24 hours. In some patients the effects may diminish toward the end of the dosing interval (see DOSAGE AND ADMINISTRATION, Hypertension).

In some patients achievement of optimal blood pressure reduction may require several weeks of therapy.

The antihypertensive effects of VASOTEC have continued during long-term therapy. Abrupt withdrawal of VASOTEC has not been associated with a rapid increase in blood pressure.

In hemodynamic studies in patients with essential hypertension, blood pressure reduction was accompanied by a reduction in peripheral arterial resistance with an increase in cardiac output and little or no change in heart rate. Following administration of VASOTEC, there is an increase in renal blood flow; glomerular filtration rate is usually unchanged. The effects appear to be similar in patients with renovascular hypertension.

When given together with thiazide-type diuretics, the blood pressure lowering effects of VASOTEC are approximately additive.

In a clinical pharmacology study, indomethacin or sulindac was administered to hypertensive patients receiving VASOTEC. In this study there was no evidence of a blunting of the antihypertensive action of VASOTEC (see PRECAUTIONS, Drug Interactions).

Heart Failure

In trials in patients treated with digitalis and diuretics, treatment with enalapril resulted in decreased systemic vascular resistance, blood pressure, pulmonary capillary wedge pressure and heart size, and increased cardiac output and exercise tolerance. Heart rate was unchanged or slightly reduced, and mean ejection fraction was unchanged or increased. There was a beneficial effect on severity of heart failure as measured by the New York Heart Association (NYHA) classification and on symptoms of dyspnea and fatigue. Hemodynamic effects were observed after the first dose and appeared to be maintained in uncontrolled studies lasting as long as four months. Effects on exercise tolerance, heart size, and severity and symptoms of heart failure were observed in placebo-controlled studies lasting from eight weeks to over one year.

Heart Failure, Mortality Trials

In a multicenter, placebo-controlled clinical trial, 2,569 patients with all degrees of symptomatic heart failure and ejection fraction ≤35 percent were randomized to placebo or enalapril and followed for up to 55 months (SOLVD-Treatment). Use of enalapril was associated with an 11 percent reduction in all-cause mortality and a 30 percent reduction in hospitalization for heart failure. Diseases that excluded patients from enrollment in the study included severe stable angina (>2 attacks/day), hemodynamically significant valvular or outflow tract obstruction, renal failure (creatinine >2.5 mg/dL), cerebrovascular disease (e.g., significant carotid artery disease), advanced pulmonary disease, malignancies, active myocarditis and constrictive pericarditis. The mortality benefit associated with enalapril does not appear to depend upon digitalis being present.

A second multicenter trial used the SOLVD protocol for study of asymptomatic or minimally symptomatic patients. SOLVD-Prevention patients, who had left ventricular ejection fraction ≤35% and no history of symptomatic heart failure, were randomized to placebo (n=2117) or enalapril (n=2111) and followed for up to 5 years. The majority of patients in the SOLVD-Prevention trial had a history of ischemic heart disease. A history of myocardial infarction was present in 80 percent of patients, current angina pectoris in 34 percent, and a history of hypertension in 37 percent. No statistically significant mortality effect was demonstrated in this population. Enalapril-treated subjects had 32% fewer first hospitalizations for heart failure, and 32% fewer total heart failure hospitalizations. Compared to placebo, 32 percent fewer patients receiving enalapril developed symptoms of overt heart failure. Hospitalizations for cardiovascular reasons were also reduced. There was an insignificant reduction in hospitalizations for any cause in the enalapril treatment group (for enalapril vs. placebo, respectively, 1166 vs. 1201 first hospitalizations, 2649 vs. 2840 total hospitalizations), although the study was not powered to look for such an effect.

The SOLVD-Prevention trial was not designed to determine whether treatment of asymptomatic patients with low ejection fraction would be superior, with respect to preventing hospitalization, to closer follow-up and use of enalapril at the earliest sign of heart failure. However, under the conditions of follow-up in the SOLVD-Prevention trial (every 4 months at the study clinic; personal physician as needed), 68% of patients on placebo who were hospitalized for heart failure had no prior symptoms recorded which would have signaled initiation of treatment.

The SOLVD-Prevention trial was also not designed to show whether enalapril modified the progression of underlying heart disease.

In another multicenter, placebo-controlled trial (CONSENSUS) limited to patients with NYHA Class IV congestive heart failure and radiographic evidence of cardiomegaly, use of enalapril was associated with improved survival. The results are shown in the following table.

 | Survival (%)
 | Six Months | One Year
VASOTEC (n=127) | 74 | 64
Placebo (n=126) | 56 | 48

In both CONSENSUS and SOLVD-Treatment trials, patients were also usually receiving digitalis, diuretics or both.

Clinical Pharmacology in Pediatric Patients

A multiple dose pharmacokinetic study was conducted in 40 hypertensive male and female pediatric patients aged 2 months to ≤16 years following daily oral administration of 0.07 to 0.14 mg/kg enalapril maleate. At steady state, the mean effective half-life for accumulation of enalaprilat was 14 hours, and the mean urinary recovery of total enalapril and enalaprilat in 24 hours was 68% of the administered dose. Conversion of enalapril to enalaprilat was in the range of 63-76%. The overall results of this study indicate that the pharmacokinetics of enalapril in hypertensive children aged 2 months to ≤16 years are consistent across the studied age groups and consistent with pharmacokinetic historic data in healthy adults.

In a clinical study involving 110 hypertensive pediatric patients 6 to 16 years of age, patients who weighed <50 kg received either 0.625, 2.5 or 20 mg of enalapril daily and patients who weighed ≥50 kg received either 1.25, 5, or 40 mg of enalapril daily. Enalapril administered once daily lowered trough blood pressure in a dose-dependent manner. The dose-dependent antihypertensive efficacy of enalapril was consistent across all subgroups (age, Tanner stage, gender, race). However, the lowest doses studied, 0.625 mg and 1.25 mg, corresponding to an average of 0.02 mg/kg once daily, did not appear to offer consistent antihypertensive efficacy. In this study, VASOTEC was generally well tolerated.

In the above pediatric studies, enalapril maleate was given as tablets of VASOTEC and for those children and infants who were unable to swallow tablets or who required a lower dose than is available in tablet form, enalapril was administered in a suspension formulation (see DOSAGE AND ADMINISTRATION, Preparation of Suspension).

INDICATIONS AND USAGE

Hypertension

VASOTEC is indicated for the treatment of hypertension.

VASOTEC is effective alone or in combination with other antihypertensive agents, especially thiazide-type diuretics. The blood pressure lowering effects of VASOTEC and thiazides are approximately additive.

Heart Failure

VASOTEC is indicated for the treatment of symptomatic congestive heart failure, usually in combination with diuretics and digitalis. In these patients VASOTEC improves symptoms, increases survival, and decreases the frequency of hospitalization (see CLINICAL PHARMACOLOGY, Heart Failure, Mortality Trials for details and limitations of survival trials).

Asymptomatic Left Ventricular Dysfunction

In clinically stable asymptomatic patients with left ventricular dysfunction (ejection fraction ≤35 percent), VASOTEC decreases the rate of development of overt heart failure and decreases the incidence of hospitalization for heart failure (see CLINICAL PHARMACOLOGY, Heart Failure, Mortality Trials for details and limitations of survival trials).

In using VASOTEC consideration should be given to the fact that another angiotensin-converting enzyme inhibitor, captopril, has caused agranulocytosis, particularly in patients with renal impairment or collagen vascular disease, and that available data are insufficient to show that VASOTEC does not have a similar risk (see WARNINGS, Neutropenia/Agranulocytosis).

In considering use of VASOTEC, it should be noted that in controlled clinical trials ACE inhibitors have an effect on blood pressure that is less in black patients than in non-blacks. In addition, it should be noted that black patients receiving ACE inhibitors have been reported to have a higher incidence of angioedema compared to non-blacks (see WARNINGS, Head and Neck Angioedema).

CONTRAINDICATIONS

VASOTEC is contraindicated in patients who are hypersensitive to this product and in patients with a history of angioedema related to previous treatment with an angiotensin-converting enzyme inhibitor and in patients with hereditary or idiopathic angioedema.

Do not coadminister aliskiren with VASOTEC in patients with diabetes (see PRECAUTIONS, Drug Interactions).

VASOTEC is contraindicated in combination with a neprilysin inhibitor (e.g., sacubitril). Do not administer VASOTEC within 36 hours of switching to or from sacubitril/valsartan, a neprilysin inhibitor (see WARNINGS, Head and Neck Angioedema).

WARNINGS

Anaphylactoid and Possibly Related Reactions

Presumably because angiotensin-converting enzyme inhibitors affect the metabolism of eicosanoids and polypeptides, including endogenous bradykinin, patients receiving ACE inhibitors (including VASOTEC) may be subject to a variety of adverse reactions, some of them serious.

Head and Neck Angioedema

Angioedema of the face, extremities, lips, tongue, glottis and/or larynx has been reported in patients treated with angiotensin-converting enzyme inhibitors, including VASOTEC. This may occur at any time during treatment. In such cases VASOTEC should be promptly discontinued and appropriate therapy and monitoring should be provided until complete and sustained resolution of signs and symptoms has occurred. In instances where swelling has been confined to the face and lips the condition has generally resolved without treatment, although antihistamines have been useful in relieving symptoms. Angioedema associated with laryngeal edema may be fatal. Where there is involvement of the tongue, glottis or larynx, likely to cause airway obstruction, appropriate therapy, e.g., subcutaneous epinephrine solution 1:1000 (0.3 mL to 0.5 mL) and/or measures necessary to ensure a patent airway, should be promptly provided (see ADVERSE REACTIONS).

Patients receiving coadministration of ACE inhibitor and mTOR (mammalian target of rapamycin) inhibitor (e.g., temsirolimus, sirolimus, everolimus) therapy or a neprilysin inhibitor may be at increased risk for angioedema (see PRECAUTIONS).

Intestinal Angioedema: Intestinal angioedema has been reported in patients treated with ACE inhibitors. These patients presented with abdominal pain (with or without nausea or vomiting); in some cases there was no prior history of facial angioedema and C1 esterase levels were normal. The angioedema was diagnosed by procedures including abdominal CT scan or ultrasound, or at surgery, and symptoms resolved after stopping the ACE inhibitor. Intestinal angioedema should be included in the differential diagnosis of patients on ACE inhibitors presenting with abdominal pain.

Patients with a history of angioedema unrelated to ACE inhibitor therapy may be at increased risk of angioedema while receiving an ACE inhibitor (see INDICATIONS AND USAGE and CONTRAINDICATIONS).

Anaphylactoid Reactions During Desensitization

Two patients undergoing desensitizing treatment with hymenoptera venom while receiving ACE inhibitors sustained life-threatening anaphylactoid reactions. In the same patients, these reactions were avoided when ACE inhibitors were temporarily withheld, but they reappeared upon inadvertent rechallenge.

Anaphylactoid Reactions During Membrane Exposure

Anaphylactoid reactions have been reported in patients dialyzed with high-flux membranes and treated concomitantly with an ACE inhibitor. Anaphylactoid reactions have also been reported in patients undergoing low-density lipoprotein apheresis with dextran sulfate absorption.

Hypotension

Excessive hypotension is rare in uncomplicated hypertensive patients treated with VASOTEC alone. Patients with heart failure given VASOTEC commonly have some reduction in blood pressure, especially with the first dose, but discontinuation of therapy for continuing symptomatic hypotension usually is not necessary when dosing instructions are followed; caution should be observed when initiating therapy (see DOSAGE AND ADMINISTRATION). Patients at risk for excessive hypotension, sometimes associated with oliguria and/or progressive azotemia, and rarely with acute renal failure and/or death, include those with the following conditions or characteristics: heart failure, hyponatremia, high-dose diuretic therapy, recent intensive diuresis or increase in diuretic dose, renal dialysis, or severe volume and/or salt depletion of any etiology. It may be advisable to eliminate the diuretic (except in patients with heart failure), reduce the diuretic dose or increase salt intake cautiously before initiating therapy with VASOTEC in patients at risk for excessive hypotension who are able to tolerate such adjustments (see PRECAUTIONS, Drug Interactions and ADVERSE REACTIONS). In patients at risk for excessive hypotension, therapy should be started under very close medical supervision and such patients should be followed closely for the first two weeks of treatment and whenever the dose of enalapril and/or diuretic is increased. Similar considerations may apply to patients with ischemic heart or cerebrovascular disease, in whom an excessive fall in blood pressure could result in a myocardial infarction or cerebrovascular accident.

If excessive hypotension occurs, the patient should be placed in the supine position and, if necessary, receive an intravenous infusion of normal saline. A transient hypotensive response is not a contraindication to further doses of VASOTEC, which usually can be given without difficulty once the blood pressure has stabilized. If symptomatic hypotension develops, a dose reduction or discontinuation of VASOTEC or concomitant diuretic may be necessary.

Neutropenia/Agranulocytosis

Another angiotensin-converting enzyme inhibitor, captopril, has been shown to cause agranulocytosis and bone marrow depression, rarely in uncomplicated patients but more frequently in patients with renal impairment, especially if they also have a collagen vascular disease. Available data from clinical trials of enalapril are insufficient to show that enalapril does not cause agranulocytosis at similar rates. Marketing experience has revealed cases of neutropenia or agranulocytosis in which a causal relationship to enalapril cannot be excluded. Periodic monitoring of white blood cell counts in patients with collagen vascular disease and renal disease should be considered.

Hepatic Failure

Rarely, ACE inhibitors have been associated with a syndrome that starts with cholestatic jaundice and progresses to fulminant hepatic necrosis, and (sometimes) death. The mechanism of this syndrome is not understood. Patients receiving ACE inhibitors who develop jaundice or marked elevations of hepatic enzymes should discontinue the ACE inhibitor and receive appropriate medical follow-up.

Fetal Toxicity

Use of drugs that act on the renin-angiotensin system during the second and third trimesters of pregnancy reduces fetal renal function and increases fetal and neonatal morbidity and death. Resulting oligohydramnios can be associated with fetal lung hypoplasia and skeletal deformations. Potential neonatal adverse effects include skull hypoplasia, anuria, hypotension, renal failure, and death. When pregnancy is detected, discontinue VASOTEC as soon as possible. These adverse outcomes are usually associated with use of these drugs in the second and third trimester of pregnancy. Most epidemiologic studies examining fetal abnormalities after exposure to antihypertensive use in the first trimester have not distinguished drugs affecting the renin-angiotensin system from other antihypertensive agents. Appropriate management of maternal hypertension during pregnancy is important to optimize outcomes for both mother and fetus.

In the unusual case that there is no appropriate alternative to therapy with drugs affecting the renin-angiotensin system for a particular patient, apprise the mother of the potential risk to the fetus. Perform serial ultrasound examinations to assess the intra-amniotic environment. If oligohydramnios is observed, discontinue VASOTEC, unless it is considered lifesaving for the mother. Fetal testing may be appropriate, based on the week of pregnancy. Patients and physicians should be aware, however, that oligohydramnios may not appear until after the fetus has sustained irreversible injury. Closely observe infants with histories of in utero exposure to VASOTEC for hypotension, oliguria, and hyperkalemia (see PRECAUTIONS, Pediatric Use).

No teratogenic effects of enalapril were seen in studies of pregnant rats and rabbits. On a body surface area basis, the doses used were 57 times and 12 times, respectively, the maximum recommended human daily dose (MRHDD).

PRECAUTIONS

General

Aortic Stenosis/Hypertrophic Cardiomyopathy

As with all vasodilators, enalapril should be given with caution to patients with obstruction in the outflow tract of the left ventricle.

Impaired Renal Function

As a consequence of inhibiting the renin-angiotensin-aldosterone system, changes in renal function may be anticipated in susceptible individuals. In patients with severe heart failure whose renal function may depend on the activity of the renin-angiotensin-aldosterone system, treatment with angiotensin-converting enzyme inhibitors, including VASOTEC, may be associated with oliguria and/or progressive azotemia and rarely with acute renal failure and/or death (see PRECAUTIONS, Drug Interactions).

In clinical studies in hypertensive patients with unilateral or bilateral renal artery stenosis, increases in blood urea nitrogen and serum creatinine were observed in 20 percent of patients. These increases were almost always reversible upon discontinuation of enalapril and/or diuretic therapy. In such patients renal function should be monitored during the first few weeks of therapy.

Some patients with hypertension or heart failure with no apparent pre-existing renal vascular disease have developed increases in blood urea and serum creatinine, usually minor and transient, especially when VASOTEC has been given concomitantly with a diuretic. This is more likely to occur in patients with pre-existing renal impairment. Dosage reduction and/or discontinuation of the diuretic and/or VASOTEC may be required.

Evaluation of patients with hypertension or heart failure should always include assessment of renal function (see DOSAGE AND ADMINISTRATION).

Hyperkalemia

Elevated serum potassium (greater than 5.7 mEq/L) was observed in approximately one percent of hypertensive patients in clinical trials. In most cases these were isolated values which resolved despite continued therapy. Hyperkalemia was a cause of discontinuation of therapy in 0.28 percent of hypertensive patients. In clinical trials in heart failure, hyperkalemia was observed in 3.8 percent of patients but was not a cause for discontinuation.

Risk factors for the development of hyperkalemia include renal insufficiency, diabetes mellitus, and the concomitant use of potassium-sparing diuretics, potassium supplements and/or potassium-containing salt substitutes, which should be used cautiously, if at all, with VASOTEC (see Drug Interactions).

Cough

Presumably due to the inhibition of the degradation of endogenous bradykinin, persistent nonproductive cough has been reported with all ACE inhibitors, always resolving after discontinuation of therapy. ACE inhibitor-induced cough should be considered in the differential diagnosis of cough.

Surgery/Anesthesia

In patients undergoing major surgery or during anesthesia with agents that produce hypotension, enalapril may block angiotensin II formation secondary to compensatory renin release. If hypotension occurs and is considered to be due to this mechanism, it can be corrected by volume expansion.

Information for Patients

Angioedema

Angioedema, including laryngeal edema, may occur at any time during treatment with angiotensin-converting enzyme inhibitors, including enalapril. Patients should be so advised and told to report immediately any signs or symptoms suggesting angioedema (swelling of face, extremities, eyes, lips, tongue, difficulty in swallowing or breathing) and to take no more drug until they have consulted with the prescribing physician.

Hypotension

Patients should be cautioned to report lightheadedness, especially during the first few days of therapy. If actual syncope occurs, the patients should be told to discontinue the drug until they have consulted with the prescribing physician. All patients should be cautioned that excessive perspiration and dehydration may lead to an excessive fall in blood pressure because of reduction in fluid volume. Other causes of volume depletion such as vomiting or diarrhea may also lead to a fall in blood pressure; patients should be advised to consult with the physician.

Hyperkalemia

Patients should be told not to use salt substitutes containing potassium without consulting their physician.

Neutropenia

Patients should be told to report promptly any indication of infection (e.g., sore throat, fever) which may be a sign of neutropenia.

Pregnancy

Female patients of childbearing age should be told about the consequences of exposure to VASOTEC during pregnancy. Discuss treatment options with women planning to become pregnant. Patients should be asked to report pregnancies to their physicians as soon as possible.

NOTE: As with many other drugs, certain advice to patients being treated with enalapril is warranted. This information is intended to aid in the safe and effective use of this medication. It is not a disclosure of all possible adverse or intended effects.

Drug Interactions

Neprilysin Inhibitors

Patients taking concomitant neprilysin inhibitors may be at increased risk for angioedema (see WARNINGS).

Dual Blockade of the Renin-Angiotensin System (RAS)

Dual blockade of the RAS with angiotensin receptor blockers, ACE inhibitors, or aliskiren is associated with increased risks of hypotension, hyperkalemia, and changes in renal function (including acute renal failure) compared to monotherapy. Most patients receiving the combination of two RAS inhibitors do not obtain any additional benefit compared to monotherapy. In general, avoid combined use of RAS inhibitors. Closely monitor blood pressure, renal function, and electrolytes in patients on VASOTEC and other agents that affect the RAS.

Do not coadminister aliskiren with VASOTEC in patients with diabetes. Avoid use of aliskiren with VASOTEC in patients with renal impairment (GFR <60 mL/min).

Hypotension — Patients on Diuretic Therapy

Patients on diuretics and especially those in whom diuretic therapy was recently instituted, may occasionally experience an excessive reduction of blood pressure after initiation of therapy with enalapril. The possibility of hypotensive effects with enalapril can be minimized by either discontinuing the diuretic or increasing the salt intake prior to initiation of treatment with enalapril. If it is necessary to continue the diuretic, provide close medical supervision after the initial dose for at least two hours and until blood pressure has stabilized for at least an additional hour (see WARNINGS, Hypotension and DOSAGE AND ADMINISTRATION).

Agents Causing Renin Release

The antihypertensive effect of VASOTEC is augmented by antihypertensive agents that cause renin release (e.g., diuretics).

Nonsteroidal Anti-Inflammatory Agents Including Selective Cyclooxygenase-2 Inhibitors (COX-2 Inhibitors)

In patients who are elderly, volume-depleted (including those on diuretic therapy), or with compromised renal function, coadministration of NSAIDs, including selective COX-2 inhibitors, with ACE inhibitors, including enalapril, may result in deterioration of renal function, including possible acute renal failure. These effects are usually reversible. Monitor renal function periodically in patients receiving enalapril and NSAID therapy.

In a clinical pharmacology study, indomethacin or sulindac was administered to hypertensive patients receiving VASOTEC. In this study there was no evidence of a blunting of the antihypertensive action of VASOTEC. However, reports suggest that NSAIDs may diminish the antihypertensive effect of ACE inhibitors.

Other Cardiovascular Agents

VASOTEC has been used concomitantly with beta adrenergic-blocking agents, methyldopa, nitrates, calcium-blocking agents, hydralazine, prazosin and digoxin without evidence of clinically significant adverse interactions.

Agents Increasing Serum Potassium

VASOTEC attenuates potassium loss caused by thiazide-type diuretics. Potassium-sparing diuretics (e.g., spironolactone, triamterene, or amiloride), potassium supplements, or potassium-containing salt substitutes may lead to significant increases in serum potassium. Therefore, if concomitant use of these agents is indicated because of demonstrated hypokalemia, they should be used with caution and with frequent monitoring of serum potassium. Potassium-sparing agents should generally not be used in patients with heart failure receiving VASOTEC.

Lithium

Lithium toxicity has been reported in patients receiving lithium concomitantly with drugs which cause elimination of sodium, including ACE inhibitors. A few cases of lithium toxicity have been reported in patients receiving concomitant VASOTEC and lithium and were reversible upon discontinuation of both drugs. It is recommended that serum lithium levels be monitored frequently if enalapril is administered concomitantly with lithium.

Gold

Nitritoid reactions (symptoms include facial flushing, nausea, vomiting and hypotension) have been reported rarely in patients on therapy with injectable gold (sodium aurothiomalate) and concomitant ACE inhibitor therapy including VASOTEC.

mTOR (Mammalian Target of Rapamycin) Inhibitors

Patients receiving coadministration of ACE inhibitor and mTOR inhibitor (e.g., temsirolimus, sirolimus, everolimus) therapy may be at increased risk for angioedema (see WARNINGS, Head and Neck Angioedema).

Carcinogenesis, Mutagenesis, Impairment of Fertility

There was no evidence of a tumorigenic effect when enalapril was administered for 106 weeks to male and female rats at doses up to 90 mg/kg/day or for 94 weeks to male and female mice at doses up to 90 and 180 mg/kg/day, respectively. These doses are 26 times (in rats and female mice) and 13 times (in male mice) the maximum recommended human daily dose (MRHDD) when compared on a body surface area basis.

Neither enalapril maleate nor the active diacid was mutagenic in the Ames microbial mutagen test with or without metabolic activation. Enalapril was also negative in the following genotoxicity studies: rec-assay, reverse mutation assay with E. coli, sister chromatid exchange with cultured mammalian cells, and the micronucleus test with mice, as well as in an in vivo cytogenic study using mouse bone marrow.

There were no adverse effects on reproductive performance of male and female rats treated with up to 90 mg/kg/day of enalapril (26 times the MRHDD when compared on a body surface area basis).

Pregnancy

Nursing Mothers

Enalapril and enalaprilat have been detected in human breast milk. Because of the potential for serious adverse reactions in nursing infants from enalapril, a decision should be made whether to discontinue nursing or to discontinue VASOTEC, taking into account the importance of the drug to the mother.

Pediatric Use

Neonates with a History of In Utero Exposure to VASOTEC

If oliguria or hypotension occurs, direct attention toward support of blood pressure and renal perfusion. Exchange transfusions or dialysis may be required as a means of reversing hypotension and/or substituting for disordered renal function. Enalapril, which crosses the placenta, has been removed from neonatal circulation by peritoneal dialysis with some clinical benefit, and theoretically may be removed by exchange transfusion, although there is no experience with the latter procedure.

Antihypertensive effects of VASOTEC have been established in hypertensive pediatric patients age 1 month to 16 years. Use of VASOTEC in these age groups is supported by evidence from adequate and well-controlled studies of VASOTEC in pediatric and adult patients as well as by published literature in pediatric patients (see CLINICAL PHARMACOLOGY, Clinical Pharmacology in Pediatric Patients and DOSAGE AND ADMINISTRATION).

VASOTEC is not recommended in neonates and in pediatric patients with glomerular filtration rate <30 mL/min/1.73 m^2, as no data are available.

ADVERSE REACTIONS

VASOTEC has been evaluated for safety in more than 10,000 patients, including over 1000 patients treated for one year or more. VASOTEC has been found to be generally well tolerated in controlled clinical trials involving 2987 patients. For the most part, adverse experiences were mild and transient in nature. In clinical trials, discontinuation of therapy due to clinical adverse experiences was required in 3.3 percent of patients with hypertension and in 5.7 percent of patients with heart failure. The frequency of adverse experiences was not related to total daily dosage within the usual dosage ranges. In patients with hypertension the overall percentage of patients treated with VASOTEC reporting adverse experiences was comparable to placebo.

Hypertension

Adverse experiences occurring in greater than one percent of patients with hypertension treated with VASOTEC in controlled clinical trials are shown below. In patients treated with VASOTEC, the maximum duration of therapy was three years; in placebo-treated patients the maximum duration of therapy was 12 weeks.

 | VASOTEC (n=2314) Incidence (discontinuation) | Placebo (n=230) Incidence
Body As A Whole
Fatigue | 3.0 (<0.1) | 2.6
Orthostatic Effects | 1.2 (<0.1) | 0.0
Asthenia | 1.1 (0.1) | 0.9
Digestive
Diarrhea | 1.4 (<0.1) | 1.7
Nausea | 1.4 (0.2) | 1.7
Nervous/Psychiatric
Headache | 5.2 (0.3) | 9.1
Dizziness | 4.3 (0.4) | 4.3
Respiratory
Cough | 1.3 (0.1) | 0.9
Skin
Rash | 1.4 (0.4) | 0.4

Heart Failure

Adverse experiences occurring in greater than one percent of patients with heart failure treated with VASOTEC are shown below. The incidences represent the experiences from both controlled and uncontrolled clinical trials (maximum duration of therapy was approximately one year). In the placebo-treated patients, the incidences reported are from the controlled trials (maximum duration of therapy is 12 weeks). The percentage of patients with severe heart failure (NYHA Class IV) was 29 percent and 43 percent for patients treated with VASOTEC and placebo, respectively.

 | VASOTEC (n=673) Incidence (discontinuation) | Placebo (n=339) Incidence
Body As A Whole
Orthostatic Effects | 2.2 (0.1) | 0.3
Syncope | 2.2 (0.1) | 0.9
Chest Pain | 2.1 (0.0) | 2.1
Fatigue | 1.8 (0.0) | 1.8
Abdominal Pain | 1.6 (0.4) | 2.1
Asthenia | 1.6 (0.1) | 0.3
Cardiovascular
Hypotension | 6.7 (1.9) | 0.6
Orthostatic Hypotension | 1.6 (0.1) | 0.3
Angina Pectoris | 1.5 (0.1) | 1.8
Myocardial Infarction | 1.2 (0.3) | 1.8
Digestive
Diarrhea | 2.1 (0.1) | 1.2
Nausea | 1.3 (0.1) | 0.6
Vomiting | 1.3 (0.0) | 0.9
Nervous/Psychiatric
Dizziness | 7.9 (0.6) | 0.6
Headache | 1.8 (0.1) | 0.9
Vertigo | 1.6 (0.1) | 1.2
Respiratory
Cough | 2.2 (0.0) | 0.6
Bronchitis | 1.3 (0.0) | 0.9
Dyspnea | 1.3 (0.1) | 0.4
Pneumonia | 1.0 (0.0) | 2.4
Skin
Rash | 1.3 (0.0) | 2.4
Urogenital
Urinary Tract Infection | 1.3 (0.0) | 2.4

Other serious clinical adverse experiences occurring since the drug was marketed or adverse experiences occurring in 0.5 to 1.0 percent of patients with hypertension or heart failure in clinical trials are listed below and, within each category, are in order of decreasing severity.

Body As A Whole: Anaphylactoid reactions (see WARNINGS, Anaphylactoid and Possibly Related Reactions).

Cardiovascular: Cardiac arrest; myocardial infarction or cerebrovascular accident, possibly secondary to excessive hypotension in high risk patients (see WARNINGS, Hypotension); pulmonary embolism and infarction; pulmonary edema; rhythm disturbances including atrial tachycardia and bradycardia; atrial fibrillation; palpitation, Raynaud’s phenomenon.

Digestive: Ileus, pancreatitis, hepatic failure, hepatitis (hepatocellular [proven on rechallenge] or cholestatic jaundice) (see WARNINGS, Hepatic Failure), melena, anorexia, dyspepsia, constipation, glossitis, stomatitis, dry mouth.

Hematologic: Rare cases of neutropenia, thrombocytopenia and bone marrow depression.

Musculoskeletal: Muscle cramps.

Nervous/Psychiatric: Depression, confusion, ataxia, somnolence, insomnia, nervousness, peripheral neuropathy (e.g., paresthesia, dysesthesia), dream abnormality.

Respiratory: Bronchospasm, rhinorrhea, sore throat and hoarseness, asthma, upper respiratory infection, pulmonary infiltrates, eosinophilic pneumonitis.

Skin: Exfoliative dermatitis, toxic epidermal necrolysis, Stevens-Johnson syndrome, pemphigus, herpes zoster, erythema multiforme, urticaria, pruritus, alopecia, flushing, diaphoresis, photosensitivity.

Special Senses: Blurred vision, taste alteration, anosmia, tinnitus, conjunctivitis, dry eyes, tearing.

Urogenital: Renal failure, oliguria, renal dysfunction (see PRECAUTIONS and DOSAGE AND ADMINISTRATION), flank pain, gynecomastia, impotence.

Miscellaneous: A symptom complex has been reported which may include some or all of the following: a positive ANA, an elevated erythrocyte sedimentation rate, arthralgia/arthritis, myalgia/myositis, fever, serositis, vasculitis, leukocytosis, eosinophilia, photosensitivity, rash and other dermatologic manifestations.

Angioedema: Angioedema has been reported in patients receiving VASOTEC, with an incidence higher in black than in non-black patients. Angioedema associated with laryngeal edema may be fatal. If angioedema of the face, extremities, lips, tongue, glottis and/or larynx occurs, treatment with VASOTEC should be discontinued and appropriate therapy instituted immediately (see WARNINGS, Head and Neck Angioedema).

Hypotension: In the hypertensive patients, hypotension occurred in 0.9 percent and syncope occurred in 0.5 percent of patients following the initial dose or during extended therapy. Hypotension or syncope was a cause for discontinuation of therapy in 0.1 percent of hypertensive patients. In heart failure patients, hypotension occurred in 6.7 percent and syncope occurred in 2.2 percent of patients. Hypotension or syncope was a cause for discontinuation of therapy in 1.9 percent of patients with heart failure (see WARNINGS, Hypotension).

Cough: See PRECAUTIONS, Cough.

Pediatric Patients

The adverse experience profile for pediatric patients appears to be similar to that seen in adult patients.

Clinical Laboratory Test Findings

Serum Electrolytes

Hyperkalemia (see PRECAUTIONS, Hyperkalemia), hyponatremia.

Creatinine, Blood Urea Nitrogen

In controlled clinical trials minor increases in blood urea nitrogen and serum creatinine, reversible upon discontinuation of therapy, were observed in about 0.2 percent of patients with essential hypertension treated with VASOTEC alone. Increases are more likely to occur in patients receiving concomitant diuretics or in patients with renal artery stenosis (see PRECAUTIONS, Impaired Renal Function). In patients with heart failure who were also receiving diuretics with or without digitalis, increases in blood urea nitrogen or serum creatinine, usually reversible upon discontinuation of VASOTEC and/or other concomitant diuretic therapy, were observed in about 11 percent of patients. Increases in blood urea nitrogen or creatinine were a cause for discontinuation in 1.2 percent of patients.

Hematology

Small decreases in hemoglobin and hematocrit (mean decreases of approximately 0.3 g percent and 1.0 vol percent, respectively) occur frequently in either hypertension or congestive heart failure patients treated with VASOTEC but are rarely of clinical importance unless another cause of anemia coexists. In clinical trials, less than 0.1 percent of patients discontinued therapy due to anemia. Hemolytic anemia, including cases of hemolysis in patients with G6PD deficiency, has been reported; a causal relationship to enalapril cannot be excluded.

Liver Function Tests

Elevations of liver enzymes and/or serum bilirubin have occurred (see WARNINGS, Hepatic Failure).

To report SUSPECTED ADVERSE REACTIONS, contact Bausch Health US, LLC at 1-800-321-4576 or FDA at 1-800-FDA-1088 or www.fda.gov/medwatch.

OVERDOSAGE

Limited data are available in regard to overdosage in humans.

Single oral doses of enalapril above 1,000 mg/kg and ≥1,775 mg/kg were associated with lethality in mice and rats, respectively.

The most likely manifestation of overdosage would be hypotension, for which the usual treatment would be intravenous infusion of normal saline solution.

Enalaprilat may be removed from general circulation by hemodialysis and has been removed from neonatal circulation by peritoneal dialysis (see WARNINGS, Anaphylactoid Reactions During Membrane Exposure).

DOSAGE AND ADMINISTRATION

Hypertension

In patients who are currently being treated with a diuretic, symptomatic hypotension occasionally may occur following the initial dose of VASOTEC. The diuretic should, if possible, be discontinued for two to three days before beginning therapy with VASOTEC to reduce the likelihood of hypotension (see WARNINGS, Hypotension). If the patient’s blood pressure is not controlled with VASOTEC alone, diuretic therapy may be resumed.

If the diuretic cannot be discontinued an initial dose of 2.5 mg should be used under medical supervision for at least two hours and until blood pressure has stabilized for at least an additional hour (see WARNINGS, Hypotension and PRECAUTIONS, Drug Interactions).

The recommended initial dose in patients not on diuretics is 5 mg once a day. Dosage should be adjusted according to blood pressure response. The usual dosage range is 10 to 40 mg per day administered in a single dose or two divided doses. In some patients treated once daily, the antihypertensive effect may diminish toward the end of the dosing interval. In such patients, an increase in dosage or twice daily administration should be considered. If blood pressure is not controlled with VASOTEC alone, a diuretic may be added. Concomitant administration of VASOTEC with potassium supplements, potassium salt substitutes, or potassium-sparing diuretics may lead to increases of serum potassium (see PRECAUTIONS).

Dosage Adjustment in Hypertensive Patients with Renal Impairment

The usual dose of enalapril is recommended for patients with a creatinine clearance more than 30 mL/min (serum creatinine of up to approximately 3 mg/dL). For patients with creatinine clearance less than or equal to 30 mL/min (serum creatinine more than or equal to 3 mg/dL), the first dose is 2.5 mg once daily. The dosage may be titrated upward until blood pressure is controlled or to a maximum of 40 mg daily.

Renal Status | Creatinine Clearance (mL/min) | Initial Dose (mg/day)
Normal Renal Function | >80 mL/min | 5 mg
Mild Impairment | ≤80 >30 mL/min | 5 mg
Moderate to Severe Impairment | ≤30 mL/min | 2.5 mg
Dialysis Patients [See WARNINGS, Anaphylactoid Reactions During Membrane Exposure.] |  | 2.5 mg on dialysis days [Dosage on nondialysis days should be adjusted depending on the blood pressure response.]

Heart Failure

VASOTEC is indicated for the treatment of symptomatic heart failure, usually in combination with diuretics and digitalis. In the placebo-controlled studies that demonstrated improved survival, patients were titrated as tolerated up to 40 mg, administered in two divided doses.

The recommended initial dose is 2.5 mg. The recommended dosing range is 2.5 to 20 mg given twice a day. Doses should be titrated upward, as tolerated, over a period of a few days or weeks. The maximum daily dose administered in clinical trials was 40 mg in divided doses.

After the initial dose of VASOTEC, the patient should be observed under medical supervision for at least two hours and until blood pressure has stabilized for at least an additional hour (see WARNINGS and PRECAUTIONS, Drug Interactions). If possible, the dose of any concomitant diuretic should be reduced which may diminish the likelihood of hypotension. The appearance of hypotension after the initial dose of VASOTEC does not preclude subsequent careful dose titration with the drug, following effective management of the hypotension.

Asymptomatic Left Ventricular Dysfunction

In the trial that demonstrated efficacy, patients were started on 2.5 mg twice daily and were titrated as tolerated to the targeted daily dose of 20 mg (in divided doses).

After the initial dose of VASOTEC, the patient should be observed under medical supervision for at least two hours and until blood pressure has stabilized for at least an additional hour (see WARNINGS and PRECAUTIONS, Drug Interactions). If possible, the dose of any concomitant diuretic should be reduced which may diminish the likelihood of hypotension. The appearance of hypotension after the initial dose of VASOTEC does not preclude subsequent careful dose titration with the drug, following effective management of the hypotension.

Dosage Adjustment in Patients with Heart Failure and Renal Impairment or Hyponatremia

In patients with heart failure who have hyponatremia (serum sodium less than 130 mEq/L) or with serum creatinine greater than 1.6 mg/dL, therapy should be initiated at 2.5 mg daily under close medical supervision (see DOSAGE AND ADMINISTRATION, Heart Failure, WARNINGS and PRECAUTIONS, Drug Interactions). The dose may be increased to 2.5 mg b.i.d. (twice a day), then 5 mg b.i.d (twice a day) and higher as needed, usually at intervals of four days or more if at the time of dosage adjustment there is not excessive hypotension or significant deterioration of renal function. The maximum daily dose is 40 mg.

Pediatric Hypertensive Patients

The usual recommended starting dose is 0.08 mg/kg (up to 5 mg) once daily. Dosage should be adjusted according to blood pressure response. Doses above 0.58 mg/kg (or in excess of 40 mg) have not been studied in pediatric patients (see CLINICAL PHARMACOLOGY, Clinical Pharmacology in Pediatric Patients).

VASOTEC is not recommended in neonates and in pediatric patients with glomerular filtration rate less than 30 mL/min/1.73 m^2, as no data are available.

Preparation of Suspension (for 200 mL of a 1.0 mg/mL suspension)

Add 50 mL of sodium citrate and citric acid oral solution, USP to a polyethylene terephthalate (PET) bottle containing ten 20 mg tablets of VASOTEC and shake for at least 2 minutes. Let concentrate stand for 60 minutes. Following the 60-minute hold time, shake the concentrate for an additional minute. Add 150 mL of Ora-Sweet SF to the concentrate in the PET bottle and shake the suspension to disperse the ingredients. The suspension should be refrigerated at 2° to 8°C (36° to 46°F) and can be stored for up to 30 days. Shake the suspension before each use.

HOW SUPPLIED

VASOTEC (enalapril maleate) Tablets
NDC | Strength | Quantity | Description
0187-0140-30; 0187-0140-90 | 2.5 mg | Bottles of 30 (with desiccant); Bottles of 90 (with desiccant) | White, oval shaped tablet imprinted with “VASO 2.5” and scored on one side and scored on the other.
0187-0141-30; 0187-0141-90 | 5 mg | Bottles of 30 (with desiccant); Bottles of 90 (with desiccant) | White, rounded triangle shaped tablet imprinted with “VASO 5” on one side and scored on the other.
0187-0142-30; 0187-0142-90; 0187-0142-10 | 10 mg | Bottles of 30 (with desiccant); Bottles of 90 (with desiccant); Bottles of 1,000 (with desiccant) | Rust red, rounded triangle shaped tablet imprinted with “VASO 10” on one side and scored on the other.
0187-0143-30; 0187-0143-90; 0187-0143-10 | 20 mg | Bottles of 30 (with desiccant); Bottles of 90 (with desiccant); Bottles of 1,000 (with desiccant) | Peach, rounded triangle shaped tablet imprinted with “VASO 20” on one side and scored on the other.

Storage

Store at 25°C (77°F); excursions permitted to 15° to 30°C (59° to 86°F) [see USP Controlled Room Temperature].

Keep container tightly closed.

Protect from moisture.

Dispense in a tight container as per USP, if product package is subdivided.

Distributed by:
Bausch Health US, LLC
Bridgewater, NJ 08807 USA

Manufactured by:
Bausch Health Companies Inc.
Steinbach, MB R5G 1Z7, Canada

VASOTEC is a registered trademark of Bausch Health Companies Inc. or its affiliates.

© 2025 Bausch Health Companies Inc. or its affiliates

9383006_20006000 Rev. 11/2025

PRINCIPAL DISPLAY PANEL - 2.5 mg Bottle Label

NDC 0187-0140-30

Rx Only

Vasotec®
(enalapril maleate)
Tablets

2.5 mg

30 Tablets

BAUSCH Health

PRINCIPAL DISPLAY PANEL - 5 mg Bottle Label

NDC 0187-0141-30

Rx only

Vasotec®
(enalapril maleate)
Tablets

5 mg

30 Tablets

BAUSCH Health

PRINCIPAL DISPLAY PANEL - 10 mg Bottle Label

NDC 0187-0142-30

Vasotec®
(enalapril maleate)
Tablets

10 mg

30 Tablets

BAUSCH Health

PRINCIPAL DISPLAY PANEL - 20 mg Bottle Label

NDC 0187-0143-30

Rx only

Vasotec®
(enalapril maleate)
Tablets

20 mg

30 Tablets

BAUSCH Health